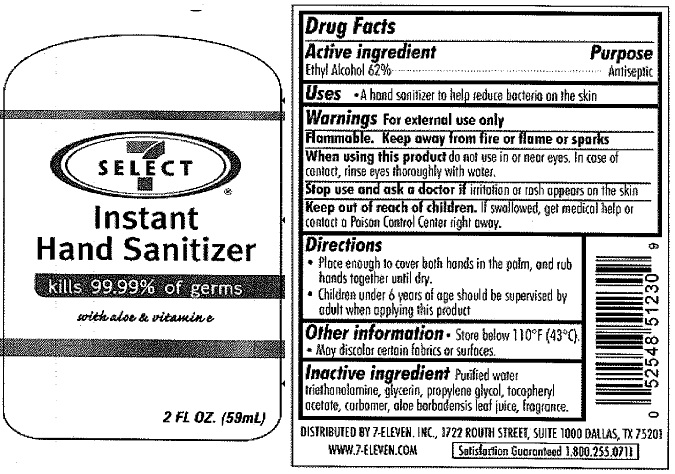 DRUG LABEL: 7-11 Instant Hand Sanitizer With Aloe And Vitamin E
NDC: 10202-085 | Form: LIQUID
Manufacturer: 7-11
Category: otc | Type: HUMAN OTC DRUG LABEL
Date: 20111102

ACTIVE INGREDIENTS: ALCOHOL 62 mL/100 mL
INACTIVE INGREDIENTS: WATER; TROLAMINE; GLYCERIN; PROPYLENE GLYCOL; ALPHA-TOCOPHEROL ACETATE; ALOE VERA LEAF; ISOPROPYL MYRISTATE

7-11 Instant Hand Sanitizer with Aloe & Vitamin E

Active Ingredient

Ethyl Alcohol 62%

Purpose

Antiseptic

Uses

- A hand sanitizer to help reduce bacteria on the skin

Warnings

Warnings For external use only

Flammable. Keep away from fire or flame or sparks

When using this product do not use in or near eyes. In case of contact, rinse eyes thoroughly with water.

Stop use and ask a doctor if irritation or rash appears on the skin.

Keep out of reach of children. If swallowed, get medical help or contact a Poison Control Center right away.

Directions

- Place enough to cover both hands in the palm, and rub hands together until dry.
- Children under 6 years of age should be supervised by adult when applying this product.

Other Information

- Store below 110 degrees F (43 degrees C)
- May discolor certain fabrics or surfaces.

Inactive Ingredient

Purified water, triethanolamine, glycerin, isopropyl myristate, propylene glycol, tocopheryl acetate, carbomer, aloe barbadensis leaf juice, fragrance.

Package Labeling

7-11

INSTANT HAND SANITIZER

WITH ALOE AND VITAMIN E

KILLS 99.99% OF GERMS

2 FL OZ (59ml)

Distributed by 7-Eleven, Inc. 1722 Routh Street, Suite 1000 Dallas TX 75201
www.7-eleven.com
Satisfaction Guaranteed 1.800.255.0711